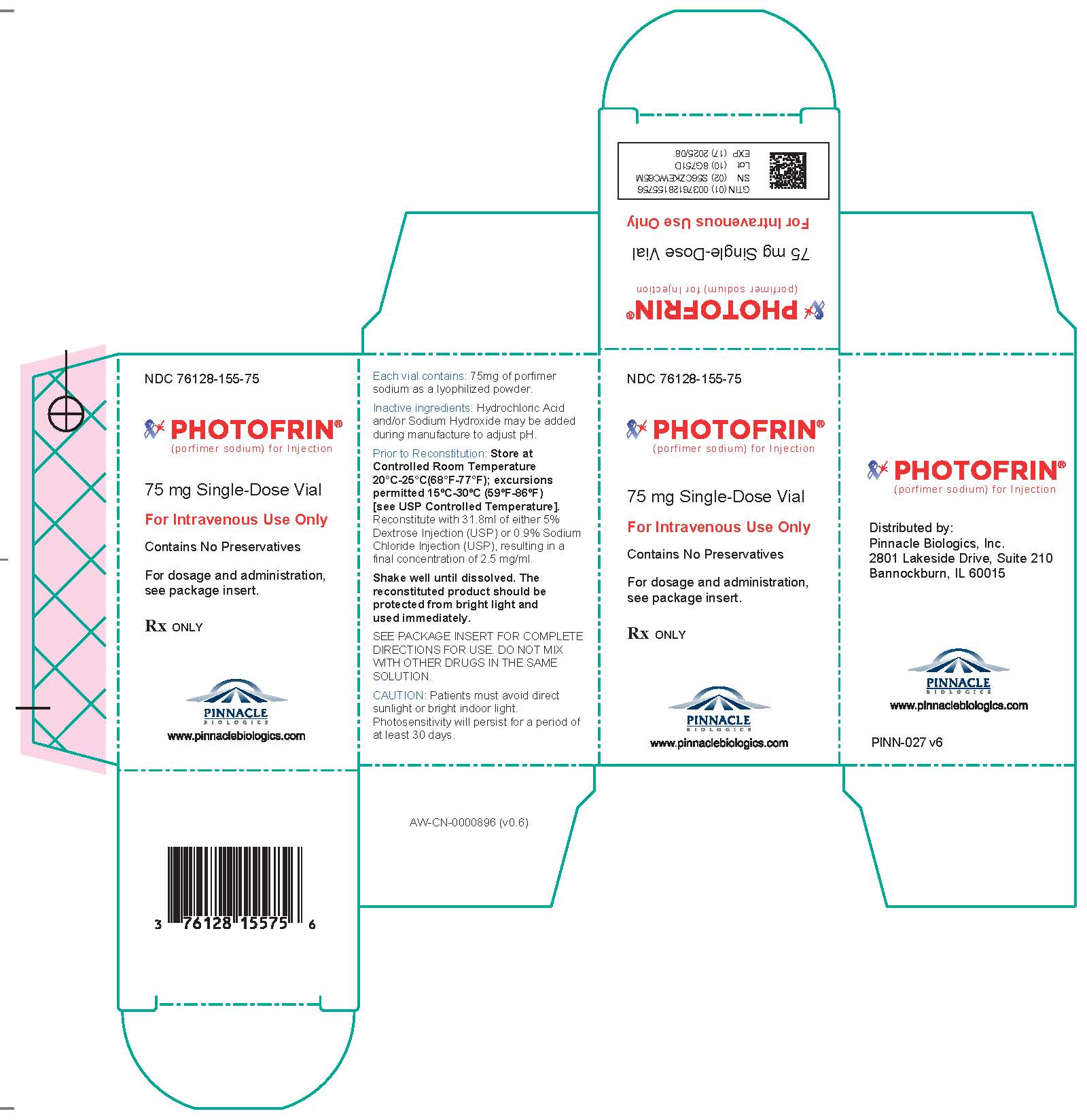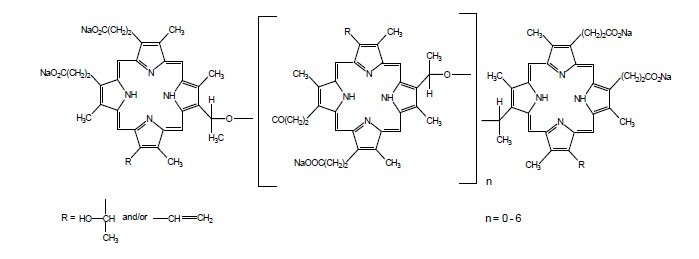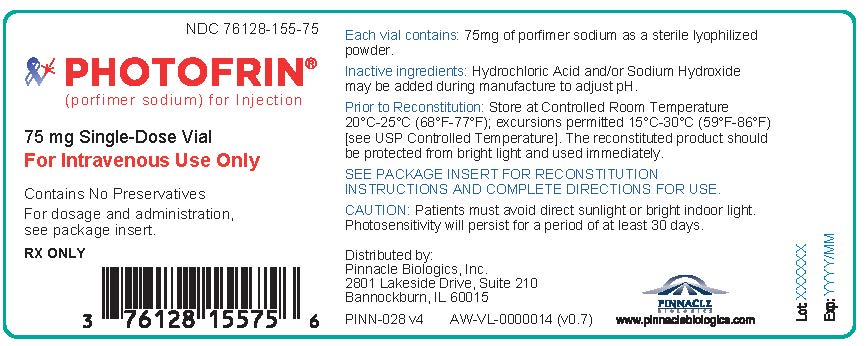 DRUG LABEL: Photofrin
NDC: 76128-155 | Form: INJECTION, POWDER, FOR SOLUTION
Manufacturer: Pinnacle Biologics, Inc.
Category: prescription | Type: Human Prescription Drug Label
Date: 20250101

ACTIVE INGREDIENTS: PORFIMER SODIUM 75 mg/31.8 mL

HIGHLIGHTS OF PRESCRIBING INFORMATION

These highlights do not include all the information needed to use PHOTOFRIN ® safely and effectively. See full prescribing information for PHOTOFRIN.
PHOTOFRIN (porfimer sodium) for injection, for intravenous use
Initial U.S. Approval: 1995

RECENT MAJOR CHANGES

Warnings and Precautions, Embryo-Fetal Toxicity (5.12) 12/2019

1 INDICATIONS AND USAGE

PHOTOFRIN is a photoactivated radical generator indicated for:

Esophageal Cancer (1.1)

- Palliation of patients with completely obstructing esophageal cancer, or of patients with partially obstructing esophageal cancer who, in the opinion of their physician, cannot be satisfactorily treated with Nd:YAG laser therapy

Endobronchial Cancer (1.2)

- Treatment of microinvasive endobronchial non-small-cell lung cancer (NSCLC) in patients for whom surgery and radiotherapy are not indicated
- Reduction of obstruction and palliation of symptoms in patients with completely or partially obstructing endobronchial NSCLC

High-Grade Dysplasia in Barrett’s Esophagus (1.3)

- Ablation of high-grade dysplasia (HGD) in Barrett’s esophagus (BE) patients who do not undergo esophagectomy

2 DOSAGE AND ADMINISTRATION

PHOTOFRIN (2.1)

- PHOTOFRIN administration: 2 mg/kg intravenous

Photoactivation (2.2)
Esophageal Cancer

- Laser light dose of 300 J/cm of fiber optic diffuser length 40–50 hours following injection with PHOTOFRIN; repeated, if needed, 96-120 hours after initial injection

Endobronchial Cancer

- Laser light dose of 200 J/cm of fiber optic diffuser length 40–50 hours following injection with PHOTOFRIN; repeated, if needed, after gentle debridement of residual tumor 96-120 hours after initial injection

High-Grade Dysplasia in Barrett’s Esophagus

- Laser light dose of 130 J/cm of fiber optic diffuser length 40–50 hours following injection with PHOTOFRIN; repeated, if needed, with a light dose of 50 J/cm of fiber optic diffuser length 96-120 hours after initial injection

3 DOSAGE FORMS AND STRENGTHS

For injection: 75 mg porfimer sodium as a lyophilized powder in single-dose vial for reconstitution (3)

4 CONTRAINDICATIONS

- Porphyria (4)
- Existing tracheoesophageal or bronchoesophageal fistula (4, 5.1)
- Tumors eroding into a major blood vessel (4, 5.2)
- Emergency treatment of patients with severe acute respiratory distress caused by an obstructing endobronchial lesion because 40 to 50 hours are required between injection of PHOTOFRIN and laser light treatment (4)
- Esophageal or gastric varices or esophageal ulcers >1 cm in diameter (4)

5 WARNINGS AND PRECAUTIONS

- Gastroesophageal Fistula and Perforation: Do not initiate PHOTOFRIN with photodynamic therapy (PDT) in patients with esophageal tumors eroding into the trachea or bronchial tree or bronchial wall. (5.1)
- Pulmonary and Gastroesophageal Hemorrhage: Assess patients for tumors eroding into a pulmonary blood vessel and esophageal varices. Do not administer light directly to an area with esophageal varices. (5.2)
- High-Grade Dysplasia (HGD) in Barrett’s Esophagus (BE): After treatment of HGD in BE, conduct endoscopic biopsy surveillance every 3 months, until 4 consecutive negative evaluations for HGD have been recorded. (5.3)
- Photosensitivity and Ocular Photosensitivity: Observe precautions to avoid exposure of skin and eyes to direct sunlight or bright indoor light for at least 30 days. Instruct patients when outdoors to wear dark sunglasses which have an average light transmittance of <4% for at least 30 days and until ocular sensitivity resolves. (5.4, 5.5)
- Use Before or After Radiotherapy: Allow 2-4 weeks between PDT and subsequent radiotherapy. (5.6)
- Chest Pain: Substernal chest pain can occur (5.7)
- Airway Obstruction and Respiratory Distress: Administer with caution to patients with tumors in locations where treatment- induced inflammation can obstruct the main airway. Monitor patients closely between the laser light therapy and the mandatory debridement bronchoscopy for any evidence of respiratory distress. (5.8)
- Esophageal Strictures: Esophageal strictures can occur (5.9)
- Hepatic and Renal Impairment: Patients with hepatic or renal impairment may need longer precautionary measures for photosensitivity. (5.10)
- Thromboembolism: Thromboembolic events can occur. (5.11)
- Embryo-Fetal Toxicity: May cause embryo-fetal toxicity. Advise females of reproductive potential of the potential risk to a fetus and to use effective contraception. (5.12, 8.1)

6 ADVERSE REACTIONS

Most common adverse reactions (>10%) are

- Esophageal Cancer: Anemia, pleural effusion, pyrexia, constipation, nausea, chest pain, pain, abdominal pain, dyspnea, photosensitivity reaction, pneumonia, vomiting, insomnia, back pain, pharyngitis (6.1)
- Obstructing Endobronchial Cancer: Dyspnea, photosensitivity reaction, hemoptysis, pyrexia, cough, pneumonia (6.1)
- Superficial Endobronchial Tumors: Exudate, photosensitivity reaction, bronchial obstruction, edema, bronchostenosis (6.1)
- High-Grade Dysplasia in Barrett’s Esophagus: Photosensitivity reaction, esophageal stenosis, vomiting, chest pain, nausea, pyrexia, constipation, dysphagia, abdominal pain, pleural effusion, dehydration (6.1)

To report SUSPECTED ADVERSE REACTIONS, contact Pinnacle Biologics, Inc. at 1-866-248-2039 or FDA at 1-800-FDA-1088 or www.fda.gov/medwatch

7 DRUG INTERACTIONS

- Other Photosensitizing Agents: May increase the risk of photosensitivity reaction (7.1)

8 USE IN SPECIFIC POPULATIONS

- Lactation: Advice not to breastfeed. (8.2)

FULL PRESCRIBING INFORMATION

1 INDICATIONS AND USAGE

1.1 Esophageal Cancer

PHOTOFRIN ® is indicated for the palliation of patients with completely obstructing esophageal cancer, or of patients with partially obstructing esophageal cancer who, in the opinion of their healthcare provider, cannot be satisfactorily treated with Nd:YAG laser therapy.

1.2 Endobronchial Cancer

PHOTOFRIN is indicated for the treatment of microinvasive endobronchial non-small-cell lung cancer (NSCLC) in patients for whom surgery and radiotherapy are not indicated.

PHOTOFRIN is indicated for the reduction of obstruction and palliation of symptoms in patients with completely or partially obstructing endobronchial NSCLC.

1.3 High-Grade Dysplasia in Barrett’s Esophagus

PHOTOFRIN is indicated for the ablation of high-grade dysplasia in Barrett’s esophagus patients who do not undergo esophagectomy.

2 DOSAGE AND ADMINISTRATION

2.1 Important Administration Instructions

Photodynamic therapy (PDT) with PHOTOFRIN is a two-stage process requiring administration of both drug and light. The first stage of PDT is the intravenous injection of PHOTOFRIN at 2 mg/kg. Illumination with laser light 40–50 hours following injection with PHOTOFRIN constitutes the second stage of therapy. A second laser light application may be given 96-120 hours after injection [see Dosage and Administration (2.2)] .

In clinical studies on endobronchial cancer, debridement via endoscopy was required 2-3 days after the initial light application. Standard endoscopic techniques are used for light administration and debridement. Healthcare providers should be fully familiar with the patient’s condition and trained in the safe and efficacious treatment of esophageal or endobronchial cancer, or high-grade dysplasia (HGD) in Barrett’s esophagus (BE) using PDT with PHOTOFRIN and associated light delivery devices. PDT with PHOTOFRIN should be applied only in those facilities properly equipped for the procedure.

The laser system must be approved for delivery of a stable power output at a wavelength of 630 ± 3 nm. Light is delivered to the tumor by cylindrical OPTIGUIDE™ fiber optic diffusers passed through the operating channel of an endoscope/bronchoscope. Instructions for use of the fiber optic and the selected laser system should be read carefully before use. OPTIGUIDE™ cylindrical diffusers are available in several lengths. The choice of diffuser tip length depends on the length of the tumor or Barrett’s mucosa to be treated. Diffuser length should be sized to avoid exposure of nonmalignant tissue to light and to prevent overlapping of previously treated malignant tissue. Refer to the OPTIGUIDE™ instructions for use for complete instructions concerning the fiber optic diffuser.

2.2 PHOTOFRIN

Recommended Dosage

The recommended dosage of PHOTOFRIN is 2 mg/kg of body weight administered as a single slow intravenous injection over 3 to 5 minutes.

Preparation and Administration

Reconstitute each vial of PHOTOFRIN with 31.8 mL of either 5% Dextrose Injection (USP) or 0.9% Sodium Chloride Injection (USP), resulting in a final concentration of 2.5 mg/mL. Shake well until dissolved. Do not mix PHOTOFRIN with other drugs in the same solution. Discard unused portion.

PHOTOFRIN reconstituted with 5% Dextrose Injection (USP) or with 0.9% Sodium Chloride Injection (USP), has a pH in the range of 7 to 8. PHOTOFRIN has been formulated with an overage to deliver the 75 mg labeled quantity. The reconstituted product should be protected from bright light and used immediately.
Reconstituted PHOTOFRIN is an opaque solution, in which detection of particulate matter by visual inspection is extremely difficult. Reconstituted PHOTOFRIN however, like all parenteral drug products, should be inspected visually for particulate matter and discoloration prior to administration whenever solution and container permit.

Management of Extravasation

Precautions should be taken to present extravasation at the injection site. If extravasation occurs, care must be taken to protect the area from light. There is no known benefit from injecting the extravasation site with another substance.

2.3 Photoactivation

Esophageal Cancer

Initiate 630 nm wavelength laser light delivery to the patient 40-50 hours following injection with PHOTOFRIN. A second laser light treatment may be given as early as 96 hours or as late as 120 hours after the initial injection with PHOTOFRIN. No further injection of PHOTOFRIN should be given for such retreatment with laser light. Before providing a second laser light treatment, the residual tumor may be debrided. The debridement is optional since the residua will be removed naturally by peristaltic action of the esophagus. Vigorous debridement may cause tumor bleeding.

Photoactivation of PHOTOFRIN is controlled by the total light dose delivered. In the treatment of esophageal cancer, a light dose of 300 Joules/cm (J/cm) of diffuser length should be delivered. The total power output at the fiber tip is set to deliver the appropriate light dose using exposure times of 12 minutes and 30 seconds. For the treatment of esophageal cancer, patients may receive a second course of PDT a minimum of 30 days after the initial therapy; up to three courses of PDT (each separated by a minimum of 30 days) can be given. Before each course of treatment, patients with esophageal cancer should be evaluated for the presence of a tracheoesophageal or bronchoesophageal fistula [see Contraindications (4)]. All patients should be evaluated for the possibility that the tumor may be eroding into a major blood vessel [see Contraindications (4)].

Endobronchial Cancer

Initiate 630 nm wavelength laser light delivery to the patient 4050 hours following injection with PHOTOFRIN. A second laser light treatment may be given as early as 96 hours or as late as 120 hours after the initial injection with PHOTOFRIN. No further injection of PHOTOFRIN should be given for such retreatment with laser light. Before providing a second laser light treatment, the residual tumor should be debrided. Vigorous debridement may cause tumor bleeding. For endobronchial tumors, debridement of necrotic tissue should be discontinued when the volume of bleeding increases, as this may indicate that debridement has gone beyond the zone of the PDT effect.

Photoactivation of PHOTOFRIN is controlled by the total light dose delivered. In the treatment of endobronchial cancer, a light dose of 200 J/cm of diffuser length should be delivered. The total power output at the fiber tip is set to deliver the appropriate light dose using exposure times of 8 minutes and 20 seconds. For noncircumferential endobronchial tumors that are soft enough to penetrate, interstitial fiber placement is preferred to intraluminal activation, since this method produces better efficacy and results in less exposure of the normal bronchial mucosa to light. It is important to perform a debridement 2 to 3 days after each light administration to minimize the potential for obstruction caused by necrotic debris [see Warnings and Precautions (5.8)].

For the treatment of endobronchial cancer, patients may receive a second course of PDT a minimum of 30 days after the initial therapy; up to three courses of PDT (each separated by a minimum of 30 days) can be given. In patients with endobronchial lesions who have recently undergone radiotherapy, sufficient time (approximately 4 weeks) should be allowed between the therapies to ensure that the acute inflammation produced by radiotherapy has subsided prior to PDT [see Warnings and Precautions (5.6)]. All patients should be evaluated for the possibility that the tumor may be eroding into a major blood vessel [see Contraindications (4)].

High-Grade Dysplasia (HGD) in Barretts Esophagus (BE)

Prior to initiating treatment with PHOTOFRIN PDT, the diagnosis of HGD in BE should be confirmed by an expert GI pathologist. Approximately 40-50 hours after PHOTOFRIN administration light should be delivered by a X-Cell Photodynamic Therapy (PDT) Balloon with Fiber Optic Diffuser. The choice of fiber optic/balloon diffuser combination will depend on the length of Barretts mucosa to be treated (Table 1).

TABLE 1. Fiber Optic Diffuser/Balloon Combination*
Treated Barrett's Mucosa Length (cm) | Fiber Optic Diffuser Length (cm) | Balloon Window Length (cm)
6-7 | 9 | 7
4-5 | 7 | 5
1-3 | 5 | 3
*Whenever possible, the BE segment selected for treatment should include normal tissue margins of a few millimeters at the proximal and distal ends.

Photoactivation is controlled by the total light dose delivered. The objective is to expose and treat all areas of HGD and the entire length of BE. The light dose administered will be 130 J/cm of diffuser length using a centering balloon. Based on the randomized clinical study, acceptable light intensity for the balloon/diffuser combinations range from 200-270 mW/cm of diffuser length.

To calculate the light dose, the following specific light dosimetry equation applies for all fiber optic diffusers:

Light Dose (J/cm) = | Power Output From Diffuser (W) x Treatment Time (s)
 | Diffuser Length (cm)

Table 2 provides the settings that will be used to deliver the dose within the shortest time (light intensity of 270 mW/cm). A second option (light intensity of 200 mW/cm) has also been included where necessary to accommodate lasers with a total capacity that does not exceed 2.5 W.

TABLE 2. Fiber Optic Power Outputs and Treatment Times Required to Deliver 130 J/cm of Diffuser Length Using the Centering Balloon
Balloon Window Length (cm) | Fiber Optic Diffuser Length (cm) | Light Intensity (mW/cm) | Required Power output from Diffuser [As measured by immersing the diffuser into the cuvet in the power meter and slowly increasing the laser power.] (mW) | Treatment Time
Balloon Window Length (cm) | Fiber Optic Diffuser Length (cm) | Light Intensity (mW/cm) | Required Power output from Diffuser [As measured by immersing the diffuser into the cuvet in the power meter and slowly increasing the laser power.] (mW) | (sec) | (min:sec)
3 | 5 | 270 | 1 350 | 480 | 8:00
5 | 7 | 270 | 1 900 | 480 | 8:00
7 | 9 | 270 | 2 440 | 480 | 8:00
 |  | 200 | 1 800 | 480 | 10:50

Note: No more than 1.5 times the required diffuser power output should be needed from the laser. If more than this is required, the system should be checked.

Short fiber diffusers (2.5 cm) are to be used to pretreat nodules with 50 J/cm of diffuser length prior to regular balloon treatment in the first laser light session or for the treatment of skip areas (i.e., an area that does not show sufficient mucosal response) after the first light session. For this treatment, the fiber optic diffuser is used without a centering balloon, and a light intensity of 400 mW/cm should be used. For nodule pretreatment and treatment of skipped areas, care should be taken to minimize exposure to normal tissue as it is also sensitized. Table 3 lists appropriate fiber optic power outputs and treatment times using a light intensity of 400 mW/cm.

TABLE 3.Short Fiber Optic Diffusers to be Used Without a Centering Balloon to Deliver 50 J/cm of Diffuser Length at a Light Intensity of 400 mW/cm
Fiber Optic Diffuser Length (cm) | Required Power Output From Diffuser [As measured by immersing the diffuser into the cuvet in the power meter and slowly increasing the laser power.] (mw) | Treatment Time (sec) | Treatment Time (min:sec)
1.0 | 400 | 125 | 2:05
1.5 | 600 | 125 | 2:05
2.0 | 800 | 125 | 2:05
2.5 | 1000 | 125 | 2:05

Note: No more than 1.5 times the required diffuser power output should be needed from the laser. If more than this is required, the system should be checked.

A maximum of 7 cm of esophageal mucosa is treated at the first light session using an appropriate size of centering balloon and fiber optic diffuser (Table 1). Whenever possible, the segment selected for the first light application should contain all the areas of HGD. Also, whenever possible, the BE segment selected for the first light application should include normal tissue margin of a few millimeters at the proximal and distal ends.

Nodules are to be pretreated at a light dose of 50 J/cm of diffuser length with a short (2.5 cm) fiber optic diffuser placed directly against the nodule followed by standard balloon application as described above.

Repeat Light Application

A second laser light application may be given to a previously treated segment that shows a skip area, using a short, 2.5 cm, fiber optic diffuser without centering balloon at the light dose of 50 J/cm of the diffuser length. Patients with BE >7 cm, should have the remaining untreated length of Barretts epithelium treated with a second PDT course at least 90 days later.

The treatment regimen is summarized in Table 4.

TABLE 4. High-Grade Dysplasia in Barretts Esophagus
Procedure | Study Day | Light Delivery Devices | Treatment Intent
PHOTOFRIN | Day 1 | NA | Uptake of photosensitizer
Laser Light Application | Day 3 [Discrete nodule will receive an initial light application of 50 J/cm (using a short fiber optic diffuser without balloon) before the balloon light application.] | 3, 5 or 7 cm balloon (130 J/cm) | Photoactivation
Laser Light Application (Optional) | Day 5 | Short (2.5 cm) fiber optic diffuser (50 J/cm) | Treatment of "skip" areas only

NA: Not Applicable

For the ablation of HGD in BE, patients may receive an additional course of PDT at a minimum of 90 days after the initial therapy; up to three courses of PDT (each injection separated by a minimum of 90 days) can be given to a previously treated segment which still shows HGD, low-grade dysplasia, or Barretts metaplasia, or to a new segment if the initial Barretts segment was >7 cm in length. Both residual and additional segments may be treated in the same light session(s) provided that the total length of the segments treated with the balloon/ diffuser combination is not greater than 7 cm. In the case of a previously treated esophageal segment, if it has not sufficiently healed and/or histological assessment of biopsies is not clear, the subsequent course of PDT may be delayed for an additional 1-2 months.

3 DOSAGE FORMS AND STRENGTHS

For injection: 75 mg of porfimer sodium as a lyophilized powder in a single-dose vial for reconstitution.

4 CONTRAINDICATIONS

- PHOTOFRIN is contraindicated in patients with porphyria.
- Photodynamic therapy (PDT) is contraindicated in patients with an existing tracheoesophageal or bronchoesophageal fistula.
- PDT is contraindicated in patients with tumors eroding into a major blood vessel.
- PDT is not suitable for emergency treatment of patients with severe acute respiratory distress caused by an obstructing endobronchial lesion because 40 to 50 hours are required between injection with PHOTOFRIN and laser light treatment.
- PDT is not suitable for patients with esophageal or gastric varices, or patients with esophageal ulcers >1 cm in diameter.

5 WARNINGS AND PRECAUTIONS

5.1 Gastroesophageal Fistula and Perforation

Serious and sometimes fatal gastrointestinal and esophageal necrosis and perforation can occur following treatment with PHOTOFRIN with PDT. Do not initiate PHOTOFRIN with PDT in patients with esophageal tumors eroding into the trachea or bronchial tree or bronchial wall because of the high likelihood of tracheoesophageal or bronchoesophageal fistula.

5.2 Pulmonary and Gastroesophageal Hemorrhage

Patients with large, centrally located tumors, cavitating tumors, or extensive tumors extrinsic to the bronchus are at high risk for fatal massive hemoptysis. Assess patients for tumors eroding into a pulmonary blood vessel [see Contraindications (4)] and esophageal varices. Do not administer light directly to an area with esophageal varices because of the high risk of hemorrhage.

5.3 High-Grade Dysplasia (HGD) in Barrett’s Esophagus (BE)

The long-term effect of PDT on HGD in BE is unknown. There is always a risk of cancer or abnormal epithelium that is invisible to the endoscopist beneath the new squamous cell epithelium; these facts emphasize the risk of overlooking cancer in such patients and the need for rigorous continuing surveillance despite the endoscopic appearance of complete squamous cell reepithelialization. Conduct endoscopic biopsy surveillance every 3 months, until 4 consecutive negative evaluations for HGD have been recorded; further follow-up may be scheduled every 6 to 12 months, as per judgment of healthcare providers. The follow-up period of the randomized study at the time of analysis was a minimum of 2 years (range 2 to 5.6 years).

5.4 Photosensitivity

All patients who receive PHOTOFRIN will be photosensitive and must observe precautions to avoid exposure of skin and eyes to direct sunlight or bright indoor light (from examination lamps, including dental lamps, operating room lamps, unshaded light bulbs at close proximity, etc.) for at least 30 days. Some patients may remain photosensitive for up to 90 days or more. The photosensitivity is due to residual drug, which will be present in all parts of the skin. Exposure of the skin to ambient indoor light is, however, beneficial because the remaining drug will be inactivated gradually and safely through a photobleaching reaction.

Therefore, patients should not stay in a darkened room during this period and should be encouraged to expose their skin to ambient indoor light. The level of photosensitivity will vary for different areas of the body, depending on the extent of previous exposure to light. Before exposing any area of skin to direct sunlight or bright indoor light, the patient should test it for residual photosensitivity. A small area of skin should be exposed to sunlight for 10 minutes. If no photosensitivity reaction (erythema, edema, blistering) occurs within 24 hours, the patient can gradually resume normal outdoor activities, initially continuing to exercise caution and gradually allowing increased exposure. If some photosensitivity reaction occurs with the limited skin test, the patient should continue precautions for another 2 weeks before retesting. The tissue around the eyes may be more sensitive, and therefore, it is not recommended that the face be used for testing. If patients travel to a different geographical area with greater sunshine, they should retest their level of photosensitivity.

Conventional ultraviolet (UV) sunscreens will only protect against UV light-related photosensitivity and will be of no value in protecting against induced photosensitivity reactions caused by visible light.

5.5 Ocular Sensitivity

Sensitivity to sun, bright lights, or car headlights, causing ocular discomfort, can occur in patients who receive PHOTOFRIN. For at least 30 days and until ocular sensitivity resolves, instruct patients when outdoors to wear dark sunglasses which have an average white light transmittance of <4%.

5.6 Use Before or After Radiotherapy

If PDT is to be used before or after radiotherapy, allot sufficient time between the two therapies to ensure that the inflammatory response produced by the first treatment has subsided before commencing the second treatment. The inflammatory response from PDT will depend on tumor size and extent of surrounding normal tissue that receives light. Allow 2 to 4 weeks after PDT before commencing radiotherapy.

The acute inflammatory reaction from radiotherapy usually subsides within 4 weeks after completing radiotherapy. Allow 4 weeks after completing radiotherapy before commencing PDT.

5.7 Chest Pain

As a result of PDT treatment, patients may complain of substernal chest pain because of inflammatory responses within the area of treatment. Such pain may be of sufficient intensity to warrant the short-term prescription of opiate analgesics.

5.8 Airway Obstruction and Respiratory Distress

PHOTOFRIN followed by PDT can cause treatment-induced inflammation and obstruct the main airway. Administer with caution to patients with endobronchial tumors in locations where treatment-induced inflammation can obstruct the main airway, e.g., long or circumferential tumors of the trachea, tumors of the carina that involve both mainstem bronchi circumferentially, or circumferential tumors in the mainstem bronchus in patients with prior pneumonectomy.

Monitor patients closely between the laser light therapy and the mandatory debridement bronchoscopy for any evidence of respiratory distress. Inflammation, mucositis, and necrotic debris may cause obstruction of the airway. If respiratory distress occurs, the physician should be prepared to carry out immediate bronchoscopy to remove secretions and debris to open the airway.

5.9 Esophageal Strictures

Esophageal strictures occurred in 122 of 318 (38%) patients enrolled in three clinical studies of patients who received PHOTOFRIN with PDT to the esophagus. Nodule pretreatment and re-treating the same mucosal segment more than once may influence the risk of developing an esophageal stricture. A total of 49% of patients who developed a stricture received nodule pretreatment and 82% who developed a stricture had a mucosal segment treated twice. Overall, esophageal strictures occurred within six months following PHOTOFRIN with PDT. Multiple dilations of esophageal strictures may be required, as shown in Table 5

TABLE 5 . Esophageal Dilations in Patients with Treatment – Related Strictures
Number of Dilations | Number of Patients With Strictures N=114 | Percentage of Patients with Strictures
1 – 2 Dilations | 32 | 28%
3 – 5 Dilations | 32 | 28%
6 - 10 | 24 | 21%
>10 Dilations | 26 | 23%

5.10 Risk of Prolonged Duration of Photosensitivity in Patients with Hepatic and Renal Impairment

Hepatic or renal impairment will likely prolong the elimination of porfimer sodium leading to higher rates of toxicity. Inform patients with severe renal impairment or mild to severe hepatic impairment that the period requiring the precautionary measures for photosensitivity may be longer than 90 days.

5.11 Thromboembolism

Thromboembolic events can occur following photodynamic therapy with PHOTOFRIN. Most reported events occurred in patients with other risk factors for thromboembolism including advanced cancer, following major surgery, prolonged immobilization, or cardiovascular disease.

5.12 Embryo-Fetal Toxicity

Based on animal studies, PHOTOFRIN may cause embryo-fetal toxicity when administered to a pregnant woman. Intravenous administration of porfimer sodium to pregnant rats and rabbits during the period of organogenesis at dose levels approximately 0.64 times the recommended human dose of PHOTOFRIN based on body surface area (BSA) resulted in increased fetal resorptions, decreased litter size, and reduced fetal weight but did not cause fetal malformations. Advise pregnant women of the potential risk to fetus. Advise females of reproductive potential and males with female partners of reproductive potential to use effective contraception during treatment with PHOTOFRIN and for 5 months after the final dose.

6 ADVERSE REACTIONS

The following clinically significant adverse reactions are described elsewhere in the labeling:

- Gastroesophageal Fistula and Perforation [see Warnings and Precautions (5.1)]
- Pulmonary and Gastroesophageal Hemorrhage [see Warnings and Precautions (5.2)]
- High-Grade Dysplasia (HGD) in Barrett’s Esophagus (BE) [see Warnings and Precautions (5.3)]
- Photosensitivity [see Warnings and Precautions (5.4)]
- Ocular Sensitivity [see Warnings and Precautions (5.5)]
- Use Before or After Radiotherapy [see Warnings and Precautions (5.6)]
- Chest Pain [see Warnings and Precautions (5.7)]
- Airway Obstruction and Respiratory Distress [see Warnings and Precautions (5.8)]
- Esophageal Strictures [see Warnings and Precautions (5.9)]
- Thromboembolism [see Warnings and Precautions (5.11)]

6.1 Clinical Trials Experience

Because clinical trials are conducted under widely varying conditions, adverse reaction rates observed in the clinical trials of a drug cannot be directly compared to rates in the clinical trials of another drug and may not reflect the rates observed in practice.

Overall Adverse Reaction Profile

Systemically induced effects of photodynamic therapy (PDT) with PHOTOFRIN consist of photosensitivity and mild constipation. All patients who receive PHOTOFRIN will be photosensitive and must observe precautions to avoid sunlight and bright indoor light [see Warnings and Precautions (5.4)].

Photosensitivity reactions occurred in approximately 20% of cancer patients and in 69% of high-grade dysplasia (HGD) in Barretts esophagus (BE) patients treated with PHOTOFRIN. Typically, these reactions were mostly mild to moderate erythema, but they also included swelling, pruritus, burning sensation, feeling hot, or blisters. In a single study of 24 healthy subjects, some evidence of photosensitivity reactions occurred in all subjects.Other less common skin manifestations were also reported in areas where photosensitivity reactions had occurred, such as increased hair growth, skin discoloration, skin nodule, skin wrinkling and increased skin fragility. These manifestations may be attributable to a pseudoporphyria state (temporary drug-induced cutaneous porphyria).

Most toxicities of this therapy are local effects seen in the region of illumination and occasionally in surrounding tissues. The local adverse reactions are characteristic of an inflammatory response induced by the photodynamic effect.

A few cases of fluid imbalance have been reported in patients treated with PHOTOFRIN PDT for overtly disseminated intraperitoneal malignancies. Fluid imbalance is an expected PDT-related event.

A case of cataracts has been reported in a 51-year-old obese man treated with PHOTOFRIN PDT for HGD in BE. The patient suffered from a PDT response with development of a deep esophageal ulcer. Within two months post PDT, the patient noted difficulty with his distant vision. A thorough eye examination revealed a change in the refractive error that later progressed to cataracts in both eyes. Both of his parents had a history of cataracts in their 70s. Whether PHOTOFRIN directly caused or accelerated a familial underlying condition is unknown.

Esophageal Carcinoma

The following adverse reactions were reported over the entire follow-up period in at least 5% of patients treated with PHOTOFRIN PDT, who had completely or partially obstructing esophageal cancer. Table 6 presents data from 88 patients who received the currently marketed formulation. The relationship of many of these adverse reactions to PDT with PHOTOFRIN is uncertain.

TABLE 6 . Adverse Reactions Reported in 5% or More of Patients* with Obstructing Esophageal Cancer
SYSTEM ORGAN CLASS (SOC) | Adverse Reaction | All Grades (%)
Patients with at Least One Adverse Reaction |  | 95
RESPIRATORY, THORACIC, and MEDIASTINAL DISORDERS | Pleural effusion | 32
RESPIRATORY, THORACIC, and MEDIASTINAL DISORDERS | Dyspnea | 20
RESPIRATORY, THORACIC, and MEDIASTINAL DISORDERS | Pneumonia | 18
RESPIRATORY, THORACIC, and MEDIASTINAL DISORDERS | Pharyngitis | 11
RESPIRATORY, THORACIC, and MEDIASTINAL DISORDERS | Respiratory insufficiency | 10
RESPIRATORY, THORACIC, and MEDIASTINAL DISORDERS | Cough | 7
RESPIRATORY, THORACIC, and MEDIASTINAL DISORDERS | Tracheoesophageal fistula | 6
BLOOD and LYMPHATIC SYSTEM DISORDERS | Anemia | 32
GENERAL DISORDERS and ADMINISTRATION SITE CONDITIONS | Pyrexia | 31
GENERAL DISORDERS and ADMINISTRATION SITE CONDITIONS | Chest pain | 22
GENERAL DISORDERS and ADMINISTRATION SITE CONDITIONS | Pain | 22
GENERAL DISORDERS and ADMINISTRATION SITE CONDITIONS | Edema Peripheral | 7
GENERAL DISORDERS and ADMINISTRATION SITE CONDITIONS | Asthenia | 6
GENERAL DISORDERS and ADMINISTRATION SITE CONDITIONS | Chest Pain (substernal) | 5
GENERAL DISORDERS and ADMINISTRATION SITE CONDITIONS | Edema generalized | 5
GASTROINTESTINAL DISORDERS | Constipation | 24
GASTROINTESTINAL DISORDERS | Nausea | 24
GASTROINTESTINAL DISORDERS | Abdominal Pain | 20
GASTROINTESTINAL DISORDERS | Vomiting | 17
GASTROINTESTINAL DISORDERS | Dysphagia | 10
GASTROINTESTINAL DISORDERS | Esophageal edema | 8
GASTROINTESTINAL DISORDERS | Hematemesis | 8
GASTROINTESTINAL DISORDERS | Dyspepsia | 6
GASTROINTESTINAL DISORDERS | Esophageal stenosis | 6
GASTROINTESTINAL DISORDERS | Diarrhea | 5
GASTROINTESTINAL DISORDERS | Esophagitis | 5
GASTROINTESTINAL DISORDERS | Eructation | 5
GASTROINTESTINAL DISORDERS | Melena | 5
SKIN and SUBCUTANEOUS TISSUE DISORDERS | Photosensitivity reaction | 19
PSYCHIATRIC DISORDERS | Insomnia | 14
PSYCHIATRIC DISORDERS | Confusional state | 8
PSYCHIATRIC DISORDERS | Anxiety | 7
MUSCULOSKELETAL and CONNECTIVE TISSUE DISORDERS | Back Pain | 11
CARDIAC DISORDERS | Atrial fibrillation | 10
CARDIAC DISORDERS | Cardiac failure | 7
CARDIAC DISORDERS | Tachycardia | 6
INFECTIONS and INFESTATIONS | Candidiasis | 9
INFECTIONS and INFESTATIONS | Urinary tract infection | 7
INVESTIGATIONS | Weight decreased | 9
METABOLISM and NUTRITION DISORDERS | Anorexia | 8
METABOLISM and NUTRITION DISORDERS | Dehydration | 7
NEOPLASMS BENIGN, MALIGNANT and UNSPECIFIED | Tumor hemorrhage | 8
VASCULAR DISORDERS | Hypotension | 7
VASCULAR DISORDERS | Hypertension | 6
INJURY, POISONING and PROCEDURAL COMPLICATIONS | Post procedural complication | 5
* Based on adverse reactions reported at any time during the entire period of follow-up.

Location of the tumor was a prognostic factor for three adverse reactions: upper-third of the esophagus (esophageal edema), middle-third (atrial fibrillation), and lower-third, the most vascular region (anemia). Also, patients with large tumors (>10 cm) were more likely to experience anemia. Two of 17 patients with complete esophageal obstruction from tumor experienced esophageal perforations, which were considered to be possibly treatment-associated; these perforations occurred during subsequent endoscopies. Serious and other notable adverse reactions observed in less than 5% of PDT-treated patients with obstructing esophageal cancer in the clinical studies include the following; their relationship to therapy is uncertain. In the gastrointestinal system, esophageal perforation, gastric ulcer, ileus, jaundice, and peritonitis have occurred. Sepsis has been reported occasionally.

Cardiovascular reactions have included angina pectoris, bradycardia, myocardial infarction, sick sinus syndrome, and supraventricular tachycardia. Respiratory reactions of bronchitis, bronchospasm, laryngotracheal edema, pneumonitis, pulmonary hemorrhage, pulmonary edema, respiratory failure, and stridor have occurred. The temporal relationship of some gastrointestinal, cardiovascular and respiratory reactions to the administration of light was suggestive of mediastinal inflammation in some patients. Vision-related reactions of abnormal vision, diplopia, eye pain and photophobia have been reported.

Obstructing Endobronchial Cancer

Table 7 presents adverse reactions that were reported over the entire follow-up period in at least 5% of patients with obstructing endobronchial cancer treated with PHOTOFRIN PDT or Nd: YAG. These data are based on the 86 patients who received the currently marketed formulation. Since it seems likely that most adverse reactions caused by these acute acting therapies would occur within 30 days of treatment, Table 7 presents those reactions occurring within 30 days of a treatment procedure, as well as those occurring over the entire follow-up period. It should be noted that follow-up was 33% longer for the PDT group than for the Nd: YAG group, thereby introducing a bias against PDT when adverse reaction rates are compared for the entire follow- up period. The extent of follow-up in the 30-day period following treatment was comparable between groups (only 9% more for PDT).

Transient inflammatory reactions in PDT-treated patients occur in about 10% of patients and manifest as pyrexia, bronchitis, chest pain, and dyspnea. The incidences of bronchitis and dyspnea were higher with PDT than with Nd: YAG. Most cases of bronchitis occurred within 1 week of treatment and all but one was mild or moderate in intensity. The reactions usually resolved within 10 days with antibiotic therapy. Treatment-related worsening of dyspnea is generally transient and self-limiting. Debridement of the treated area is mandatory to remove exudate and necrotic tissue. Life-threatening respiratory insufficiency likely due to therapy occurred in 3% of PDT-treated patients and 2% of Nd: YAG-treated patients [see Warnings and Precautions (5.8)].

There was a trend toward a higher rate of fatal massive hemoptysis (FMH) occurring on the PDT arm (10%) versus the Nd:YAG arm (5%), however, the rate of FMH occurring within 30 days of treatment was the same for PDT and Nd:YAG (4% total events, 3% treatment-associated events). Patients who have received radiation therapy have a higher incidence of FMH after treatment with PDT and after other forms of local therapy than patients who have not received radiation therapy, but analyses suggest that this increased risk may be due to associated prognostic factors such as having a centrally located tumor. The incidence of FMH in patients previously treated with radiotherapy was 21% (6/29) in the PDT group and 10% (3/29) in the Nd:YAG group. In patients with no prior radiotherapy, the overall incidence of FMH was less than 1%. Characteristics of patients at high risk for FMH are described in Contraindications (4) and Warnings and Precautions (5.2).

Other serious or notable adverse reactions were observed in less than 5% of PDT-treated patients with endobronchial cancer; their relationship to therapy is uncertain. In the respiratory system, pulmonary thrombosis, pulmonary embolism, and lung abscess have occurred. Cardiac failure, sepsis, and possible cerebrovascular accident have also been reported in one patient each.

TABLE 7. Adverse Reactions Reported in 5% or More of Patients with Obstructing Endobronchial Cancer
SYSTEM ORGAN CLASS (SOC) | Adverse Reaction | Within 30 Days of Treatment |  | Entire Follow-up Period [Follow-up was 33% longer for the PDT group than for the Nd:YAG group, introducing a bias against PDT when adverse reactions are compared for the entire follow-up period.]
SYSTEM ORGAN CLASS (SOC) | Adverse Reaction | PDT | Nd:YAG | PDT | Nd:YAG
SYSTEM ORGAN CLASS (SOC) | Adverse Reaction | % | % | % | %
Patients with at Least One Adverse Reaction |  | 50 | 38 | 72 | 56
RESPIRATORY, THORACIC and MEDIASTINAL DISORDERS | Dyspnea | 17 | 8 | 30 | 15
RESPIRATORY, THORACIC and MEDIASTINAL DISORDERS | Bronchitis | 10 | 2 | 10 | 2
RESPIRATORY, THORACIC and MEDIASTINAL DISORDERS | Hemoptysis | 7 | 6 | 16 | 8
RESPIRATORY, THORACIC and MEDIASTINAL DISORDERS | Cough | 6 | 9 | 15 | 13
RESPIRATORY, THORACIC and MEDIASTINAL DISORDERS | Pneumonia | 6 | 5 | 12 | 6
RESPIRATORY, THORACIC and MEDIASTINAL DISORDERS | Productive cough | 5 | 6 | 8 | 7
RESPIRATORY, THORACIC and MEDIASTINAL DISORDERS | Respiratory insufficiency | 0 | 0 | 6 | 1
RESPIRATORY, THORACIC and MEDIASTINAL DISORDERS | Pleural effusion | 0 | 0 | 5 | 1
RESPIRATORY, THORACIC and MEDIASTINAL DISORDERS | Pneumothorax | 0 | 0 | 0 | 5
SKIN and SUBCUTANEOUS TISSUE DISORDERS | Photosensitivity reaction | 9 | 0 | 21 | 0
GENERAL DISORDERS and ADMINISTRATION SITE CONDITIONS | Pyrexia | 8 | 8 | 16 | 9
GENERAL DISORDERS and ADMINISTRATION SITE CONDITIONS | Chest pain | 7 | 7 | 8 | 9
GENERAL DISORDERS and ADMINISTRATION SITE CONDITIONS | Edema peripheral | 3 | 3 | 5 | 3
GENERAL DISORDERS and ADMINISTRATION SITE CONDITIONS | Pain | 1 | 5 | 5 | 9
PSYCHIATRIC DISORDERS | Insomnia | 5 | 2 | 5 | 4
PSYCHIATRIC DISORDERS | Anxiety | 3 | 0 | 6 | 0
GASTROINTESTINAL DISORDERS | Constipation | 5 | 1 | 5 | 2
GASTROINTESTINAL DISORDERS | Dyspepsia | 1 | 5 | 2 | 6
MUSCULOSKELETAL and CONNECTIVE TISSUE DISORDERS | Back pain | 3 | 1 | 3 | 6
NERVOUS SYSTEM DISORDERS | Dysphonia | 3 | 2 | 5 | 2

Superficial Endobronchial Tumors

The following adverse reactions were reported over the entire follow-up period in at least 5% of patients with superficial tumors (microinvasive or carcinoma in situ) who received the currently marketed formulation.

TABLE 8. Adverse Reactions Reported in 5% or More of Patients* with Superficial Endobronchial Tumors
SYSTEM ORGAN CLASS (SOC) | Adverse Reaction | All grades (%)
Patients with at Least One Adverse Reaction |  | 49
RESPIRATORY, THORACIC and MEDIASTINAL DISORDERS | Exudate | 22
RESPIRATORY, THORACIC and MEDIASTINAL DISORDERS | Bronchial mucus plug or bronchial obstruction | 21
RESPIRATORY, THORACIC and MEDIASTINAL DISORDERS | Edema | 18
RESPIRATORY, THORACIC and MEDIASTINAL DISORDERS | Bronchostenosis | 11
RESPIRATORY, THORACIC and MEDIASTINAL DISORDERS | Bronchial ulceration | 9
RESPIRATORY, THORACIC and MEDIASTINAL DISORDERS | Cough | 9
RESPIRATORY, THORACIC and MEDIASTINAL DISORDERS | Dyspnea | 7
SKIN and SUBCUTANEOUS TISSUE DISORDERS | Photosensitivity reaction | 22
* Based on adverse reactions reported at any time during the entire period of follow-up.

In patients with superficial endobronchial tumors, 44 of 90 patients (49%) experienced an adverse reaction, two-thirds of which were related to the respiratory system. The most common reaction to therapy was a mucositis reaction in one-fifth of the patients, which manifested as edema, exudate, and obstruction. The obstruction (mucus plug) is easily removed with suction or forceps. Mucositis can be minimized by avoiding exposure of normal tissue to excessive light [see Warnings and Precautions (5.8)].

Three patients experienced life-threatening dyspnea: one was given a double dose of light, one was treated concurrently in both mainstem bronchi and the other had had prior pneumonectomy and was treated in the sole remaining main airway [see Warnings and Precautions (5.2)].

Stent placement was required in 3% of the patients due to endobronchial stricture. Fatal massive hemoptysis occurred within 30 days of treatment in one patient with superficial tumors (1%).

High-Grade Dysplasia (HGD) in Barretts Esophagus (BE)

Table 9 presents adverse reactions that were reported over the follow-up period in at least 5% of patients with HGD in BE in either controlled or uncontrolled clinical trials.

In the PHOTOFRIN PDT + omeprazole (OM) group, severe adverse reactions included chest pain of non- cardiac origin, dysphagia, nausea, vomiting, regurgitation, and heartburn. The severity of these symptoms decreased within 4 to 6 weeks following treatment.

The majority of the photosensitivity reactions occurred within 90 days following PHOTOFRIN and was of mild (68%) or moderate (24%) intensity. Fourteen (10%) patients reported severe reactions, all of which resolved. The typical reaction was described as skin disorder, sunburn or rash, and affected mostly the face, hands, and neck. Associated symptoms and signs were swelling, pruritis, erythema, blisters, burning sensation, and feeling of heat.

The majority of esophageal stenosis including strictures reported in the PHOTOFRIN PDT + OM group were of mild (57%) or moderate (35%) intensity, while approximately 8% were of severe intensity. The majority of esophageal strictures were reported during Course 2 of treatment. All esophageal strictures were considered to be due to treatment. Most esophageal strictures were manageable through dilations [see Warnings and Precautions (5.9)].

TABLE 9. Adverse Reactions Reported in >5% of Patients Treated with PHOTOFRIN PDT in the Clinical Trials on High-Grade Dysplasia in Barrett's Esophagus
SYSTEM ORGAN CLASS (SOC) | Adverse Reaction | TREATMENT GROUPS
SYSTEM ORGAN CLASS (SOC) | Adverse Reaction | HGD [Includes all HGD patients in the Safety population from PHO BAR 02 (N=133), TCSC 93-07 (N=44), and TCSC 96-01 (N=42).] PHOTOFRIN | HGD [Includes all HGD patients in the Safety population from PHO BAR 02 (N=69).] Omeprazole | Other [Includes patients with Barretts metaplasia, indefinite dysplasia, LGD, and adenocarcinoma at baseline in the Safety population from TCSC 93-07 (N=55) and TCSC 96-01 (N=44).] PHOTOFRIN | Total PHOTOFRIN
SYSTEM ORGAN CLASS (SOC) | Adverse Reaction | PDT + Omeprazole N (%) | Only N (%) | PDT + Omeprazole N (%) | PDT + Omeprazole N (%)
Patients with at Least One Adverse Reaction |  | 94 | 13 | 98 | 95
GASTROINTESTINAL DISORDERS | Gastrointestinal | 74 | 9 | 84 | 77
GASTROINTESTINAL DISORDERS | Esophageal Stricture [Esophageal stricture was defined as a dilated esophageal stenosis.] | 37 | 0 | 33 | 36
GASTROINTESTINAL DISORDERS | Esophageal Narrowing [Esophageal narrowing was defined as an undilated esophageal stenosis.] | 32 | 6 | 24 | 30
GASTROINTESTINAL DISORDERS | Vomiting | 29 | 1 | 34 | 31
GASTROINTESTINAL DISORDERS | Nausea | 26 | 1 | 62 | 37
GASTROINTESTINAL DISORDERS | Dysphagia | 22 | 0 | 26 | 24
GASTROINTESTINAL DISORDERS | Constipation | 11 | 1 | 7 | 10
GASTROINTESTINAL DISORDERS | Hiccups | 7 | 0 | 1 | 5
GASTROINTESTINAL DISORDERS | Esophageal pain | 6 | 0 | 9 | 7
GASTROINTESTINAL DISORDERS | Odynophagia | 6 | 0 | 4 | 5
GASTROINTESTINAL DISORDERS | Abdominal Pain (Upper, lower, NOS) | 5 | 1 | 6 | 5
GASTROINTESTINAL DISORDERS | Dyspepsia | 5 | 0 | 4 | 4
SKIN and SUBCUTANEOUS TISSUE DISORDERS | Skin and Subcutaneous Tissue | 53 | 1 | 28 | 45
SKIN and SUBCUTANEOUS TISSUE DISORDERS | Photosensitivity reaction | 47 | 0 | 16 | 37
GENERAL and ADMINISTRATION SITE CONDITIONS | General | 50 | 0 | 63 | 54
GENERAL and ADMINISTRATION SITE CONDITIONS | Chest pain | 29 | 0 | 37 | 31
GENERAL and ADMINISTRATION SITE CONDITIONS | Pyrexia | 19 | 0 | 13 | 17
GENERAL and ADMINISTRATION SITE CONDITIONS | Chest discomfort | 6 | 0 | 19 | 10
GENERAL and ADMINISTRATION SITE CONDITIONS | Pain | 5 | 0 | 7 | 6
RESPIRATORY, THORACIC and MEDIASTINAL DISORDERS | Respiratory | 16 | 0 | 18 | 17
RESPIRATORY, THORACIC and MEDIASTINAL DISORDERS | Pleural effusion | 10 | 0 | 15 | 12
METABOLISM and NUTRITION DISORDERS | Metabolism and Nutrition | 13 | 0 | 16 | 14
METABOLISM and NUTRITION DISORDERS | Dehydration | 11 | 0 | 8 | 10
INVESTIGATIONS | Investigations | 11 | 0 | 11 | 11
 | Weight decreased | 7 | 0 | 2 | 5
INJURY, POISONING and PROCEDURAL COMPLICATIONS | Injury and Procedural | 11 | 0 | 19 | 14
INJURY, POISONING and PROCEDURAL COMPLICATIONS | Post procedural pain | 6 | 0 | 14 | 9

NOTE: Adverse reactions classified using MedDRA 5.0 dictionary with the exception of esophageal stricture and esophageal narrowing.

Laboratory Abnormalities

In patients with esophageal cancer, PDT with PHOTOFRIN may result in anemia due to tumor bleeding. No significant effects were observed for other parameters in patients with endobronchial carcinoma or with HGD in BE.

6.2 Postmarketing Experience

The following adverse reactions have been identified during post-approval use of PHOTOFRIN with PDT. Because these reactions are reported voluntarily from a population of uncertain size, it is not always possible to reliably estimate their frequency or establish a causal relationship to drug exposure. Infusion reactions: Infusion reactions including urticaria, bradycardia, hypotension, dizziness, and hypertension.

7 DRUG INTERACTIONS

7.1 Use with Other Photosensitizing Agents

PHOTOFRIN can cause photosensitivity. The concomitant use of PHOTOFRIN with other photosensitizing agents (e.g., tetracyclines, sulfonamides, phenothiazines, sulfonylurea hypoglycemic agents, thiazide diuretics, griseofulvin, and fluoroquinolones) may increase the risk of a photosensitivity reaction. Avoid the concomitant use of PHOTOFRIN with other products known to cause photosensitivity.

8 USE IN SPECIFIC POPULATIONS

8.1 Pregnancy

Risk Summary

Based on animal studies, PHOTOFRIN may cause embryo-fetal toxicity when administered to a pregnant woman. There are no available data on PHOTOFRIN use in pregnant women to evaluate for a drug-associated risk of major birth defects, miscarriage, or adverse maternal or fetal outcomes. Intraveneous administration of porfimer sodium to pregnant rats and rabbits during the period of organogenesis at dose levels approximately 0.64 times the recommended human dose of PHOTOFRIN based on body surface area (BSA) resulted in increased fetal resorptions, decreased litter size, and reduced fetal weight, but did not cause fetal malformations.

In the U.S. general population, the estimated background risk of major birth defects and miscarriage in clinically recognized pregnancies is 2 to 4% and 15 to 20% respectively.

Data

Animal Data

Intravenous administration of porfimer sodium to pregnant rats for 10 days during the period of organogenesis at dose levels 0.64 times the recommended human dose of PHOTOFRIN based on BSA resulted in maternal and embryo-fetal toxicity resulting in increased resorptions, decreased litter size, delayed ossification, and reduced fetal weight but did not cause major fetal malformations. Intravenous administration of porfimer sodium to pregnant rabbits for 13 days during the period of organogenesis at dose levels 0.65 times the recommended human dose of PHOTOFRIN based on BSA caused maternal toxicity resulting in increased resorptions, decreased litter size, and reduced fetal body weight but did not cause major fetal malformations. Intravenous administration of porfimer sodium to rats for at least 42 days during late pregnancy (post- organogenesis, GD17-PND21) through lactation at dose levels 0.32 times the recommended human dose of PHOTOFRIN based on BSA caused a reversible decrease in growth of offspring. Parturition was unaffected.

8.2 Lactation

Risk Summary

There are no data on the presence of porfimer sodium in human or animal milk, the effects on the breastfed infant, or the effects on milk production. Because of the potential for serious adverse reactions in the breastfed infant, advise patients that breastfeeding is not recommended during treatment with PHOTOFRIN and for 5 months after the last dose.

8.3 Females and Males of Reproductive Potential

Pregnancy Testing

Verify pregnancy status in females of reproductive potential prior to the initiation of PHOTOFRIN therapy [see Use in Specific Populations (8.1)] .

Contraception

PHOTOFRIN may cause fetal harm when administered to a pregnant woman [see Use in Specific Populations (8.1)] .

Females

Advise females of reproductive potential to use effective contraception during treatment with PHOTOFRIN and for 5 months after the final dose.

Males

Advise male patients with female partners of reproductive potential to use condoms during treatment with PHOTOFRIN and for 5 months following the final dose .

8.4 Pediatric Use

Safety and effectiveness in pediatrics have not been established.

8.5 Geriatric Use

Approximately 70% of the patients treated with PDT using PHOTOFRIN in clinical trials were over 60 years of age. No overall differences in safety or effectiveness were observed between these patients compared to younger patients.

10 OVERDOSAGE

PHOTOFRIN Overdose

There is limited information on overdosages involving PHOTOFRIN. Laser treatment should not be given if an overdose of PHOTOFRIN is administered. In the event of an overdose, instruct patients to protect their eyes and skin from direct sunlight or bright indoor lights for at least 30 days and then test for residual photosensitivity [see Warnings and Precautions (5.4)] . PHOTOFRIN is not dialyzable.

Overdose of Laser Light Following PHOTOFRIN

Life-threatening dyspnea has been reported in a patient with a superficial endobronchial tumor who was administered a light dose higher than the recommended dose. Increased symptoms and damage to normal tissue might be expected following an overdose of light. There is no information on overdose of laser light following PHOTOFRIN in patients with esophageal cancer or with high-grade dysplasia in Barrett’s esophagus.

11 DESCRIPTION

Porfimer sodium is a photoactivated radical generator. Porfimer sodium is a mixture of oligomers formed by ether and ester linkages of up to eight porphyrin units. The structural formula below is representative of the components of porfimer sodium.

PHOTOFRIN (porfimer sodium) for injection, for intravenous use, is supplied in a single-dose vial as dark red to reddish brown lyophilized powder, which has a cake-like appearance. Each vial contains 75 mg of porfimer sodium. Hydrochloric acid and/ or sodium hydroxide may be added to adjust the pH to within 7.2-7.9. There are no preservatives or other additives.

12 CLINICAL PHARMACOLOGY

12.1 Mechanism of Action

The cytotoxic and antitumor actions of PHOTOFRIN are light and oxygen dependent. Photodynamic therapy (PDT) with PHOTOFRIN is a two-stage process. The first stage is the intravenous administration of PHOTOFRIN. Clearance from a variety of tissues occurs over 40-72 hours, but tumors, skin, and organs of the reticuloendothelial system (including liver and spleen) retain PHOTOFRIN for a longer period. The second stage is the illumination with 630 nm wavelength laser light. Tumor selectivity in treatment occurs through a combination of selective retention of PHOTOFRIN and selective delivery of light.

Cellular damage caused by PDT with PHOTOFRIN is a consequence of the propagation of radical reactions. Radical initiation may occur after porfimer sodium absorbs light to form a porphyrin excited state. Spin transfer from porfimer sodium to molecular oxygen may then generate singlet oxygen. Subsequent radical reactions can form superoxide and hydroxyl radicals. Tumor death also occurs through ischemic necrosis secondary to vascular occlusion that appears to be partly mediated by thromboxane A2 release. As opposed to a thermal effect, the laser treatment with porfimer sodium induces a photochemical effect. The necrotic reaction and associated inflammatory responses may evolve over several days.

12.2 Pharmacodynamics

The duration of the PDT effect of PHOTOFRIN is dependent on retention and clearance of porfimer sodium from the tumor tissue and delivery of light.

Drug Interaction Studies
Findings in animals and cell culture suggest that many drugs could influence the effect of PDT, including compounds that quench active oxygen species or scavenge free radicals; decrease clotting, vasoconstriction or platelet aggregation: glucocorticosteroids; allopurinol; calcium channel blockers; and some prostaglandin inhibitors.

12.3 Pharmacokinetics

The pharmacokinetics of porfimer sodium were studied in 18 patients with cancer who received PHOTOFRIN 2 mg/kg/dose administered as a slow intravenous infusion over 3 to 5 minutes followed by a second dose administered 30 to 45 days later. The mean C max were comparable after the first and second dose (43.1±10.5 mcg/mL and 41.3±8.7 mcg/mL, respectively). The mean AUC 0-INF was about 34% higher after the second dose compared to that after the first dose (3937±1034 mcg.h/mL and 2937±627 mcg. hour/mL, respectively), indicating some accumulation upon repeated administration.

Distribution

Clearance from a variety of tissues occurs over 40 to 72 hours, but tumors, skin, and organs of the reticuloendothelial system (including liver and spleen) retain porfimer sodium for a longer period.

Porfimer sodium was approximately 90% protein bound in human serum in vitro. The binding was independent of concentration over the concentration range of 20 to 100 mcg/mL.

Elimination

The elimination half- life is 410 hours after the first dose and increases to 725 hours after the second dose.

Specific Populations

No clinically significant differences in the pharmacokinetics of porfimer sodium were observed based on sex. The effect of renal and hepatic impairment has not been studied.

13 NONCLINICAL TOXICOLOGY

13.1 Carcinogenesis, Mutagenesis, and Impairment of Fertility

No long-term studies have been conducted to evaluate the carcinogenic potential of porfimer sodium.

In the presence of light, porfimer sodium PDT did not cause mutations in the Ames test, nor did it cause chromosome aberrations or mutations (HGPRT locus) in Chinese hamster ovary (CHO) cells in vitro. Porfimer sodium PDT caused <2-fold, but significant, increases in sister chromatid exchange in CHO cells irradiated with visible light and a 3-fold increase in Chinese hamster lung fibroblasts irradiated with near UV light.

Porfimer sodium PDT caused an increase in thymidine kinase mutants and DNA-protein cross-links in mouse L5178Y cells, but not mouse LYR83 cells. Porfimer sodium PDT caused a light-dose dependent increase in DNA-strand breaks in malignant human cervical carcinoma cells, but not in normal cells. In the absence of light, porfimer sodium was negative in a Chinese hamster ovarian cells (CHO/HGPRT) mutation test. In vivo, porfimer sodium did not cause chromosomal aberrations in the mouse micronucleus test.

Porfimer sodium given to male and female rats intravenously at 4 mg/kg/day (0.32 times the recommended human dose of PHOTOFRIN based on BSA) before conception and through Day 7 of pregnancy caused no impairment of fertility. In this study, long-term dosing with porfimer sodium caused discoloration of testes and ovaries and hypertrophy of the testes. Porfimer sodium also caused decreased body weight in the parent rats.

14 CLINICAL STUDIES

Clinical studies of photodynamic therapy (PDT) with PHOTOFRIN were conducted in patients with obstructing esophageal and endobronchial non-small-cell lung cancers (NSCLC), in patients with early-stage radiologically occult endobronchial cancer, and in patients with high-grade dysplasia (HGD) in Barrett’s esophagus (BE). In all clinical studies, the method of PDT administration was essentially identical. A course of therapy consisted of one injection of PHOTOFRIN (2 mg/kg administered as a slow intravenous infusion over 3–5 minutes) followed by up to two non-thermal applications of 630 nm laser light. Light doses of 300 J/cm of diffuser length were used in esophageal cancer. Light doses of 200 J/cm of diffuser length were used in endobronchial cancer for both palliation of obstructing cancer and treatment of superficial lesions. Light doses of 130 J/cm of diffuser length using a centering balloon for the first application and 50 J/cm of diffuser length without a centering balloon for the second application were used for HGD in BE [see Dosage and Administration (2.2)] . In all cases, the first application of light occurred 40–50 hours after PHOTOFRIN.

For treatment of esophageal cancer, optional debridement of residua could be performed via endoscopy 96-120 hours after PHOTOFRIN administration, after which any residual tumor could be retreated with a second laser light application at the same light dose used for the initial treatment. Additional courses of PDT with PHOTOFRIN were allowed after 1 month, up to a maximum of 3 courses.

For treatment of endobronchial cancer, debridement of residua was performed via bronchoscopy 96-120 hours after PHOTOFRIN administration, after which any residual tumor could be retreated with a second laser light application at the same light dose used for the initial treatment. Additional courses of PDT with PHOTOFRIN were allowed after 1 month, up to a maximum of 3 courses.

For ablation of HGD in BE, a second laser light application of 50 J/cm of diffuser length without a centering balloon could be given 96-120 hours after PHOTOFRIN administration for untreated areas (“skip” areas).
Additional courses of PDT with PHOTOFRIN were allowed after 3 months, up to a maximum of 3 courses.

14.1 Esophageal Cancer

PDT with PHOTOFRIN was utilized in a multicenter, single-arm study in 17 patients with completely obstructing esophageal carcinoma. Assessments were made at 1 week and 1 month after the last treatment procedure. As shown in Table 10, after a single course of therapy, 94% of patients obtained an objective tumor response and 76% of patients experienced some palliation of their dysphagia. On average, before treatment these patients had difficulty swallowing liquids, even saliva. After one course of therapy, there was a statistically significant improvement in mean dysphagia grade (1.5 units, p <0.05) and 13 of 17 patients could swallow liquids without difficulty 1 week and/or 1 month after treatment. Based on all courses, three patients achieved a complete tumor response (CR). In two of these patients, the CR was documented only at Week 1 as they had no further assessments. The third patient achieved a CR after a second course of therapy, which was supported by negative histopathology and maintained for the entire follow-up of 6 months.

Of the 17 treated patients, 11 (65%) received clinically important benefit from PDT. Clinically important benefit was defined hierarchically as a complete tumor response (3 patients), achievement of normal swallowing (2 patients went from Grade 5 dysphagia to Grade 1), or achievement of a marked improvement of two or more grades of dysphagia with minimal adverse reactions (6 patients). The median duration of benefit in these patients was 69 days. Duration of benefit was calculated only for the period with documented evidence of improvement. All of these patients were still in response at their last assessment and, therefore, the estimate of 69 days is conservative. The median survival for these 11 patients was 115 days.

14.2 Endobronchial Cancer

Two randomized multicenter studies were conducted to compare the safety and efficacy of PHOTOFRIN PDT versus Nd:YAG laser therapy for reduction of obstruction and palliation of symptomatic patients with partially or completely obstructing endobronchial non-small-cell lung cancer. Assessments were made at 1 week and at monthly intervals after treatment. Table 11 shows the results from all randomized patients in the two studies combined. Objective tumor response rates (CR + PR), which demonstrate reduction of obstruction, were 59% for PDT and 58% for Nd:YAG at Week 1. The response rate at 1 month or later was 60% for PDT and 41% for Nd:YAG.

Patient symptoms were evaluated using a 5- or 6-grade pulmonary symptom severity rating scale for dyspnea, cough, and hemoptysis. Patients with moderate to severe symptoms are those most in need of palliation. Improvements of 2 or more grades are considered to be clinically significant. Table 12 shows the percentages of patients with moderate to severe symptoms at baseline who demonstrated a 2-grade improvement at any time during the interval evaluated.

TABLE 10. Course 1 Efficacy Results in Patients with Completely Obstructing Esophageal Cancer
EFFICACY PARAMETER | PDT N=17
OBJECTIVE TUMOR RESPONSE [CR+PR, CR = complete response (absence of endoscopically visible tumor), PR = partial response (appearance of a visible lumen).] (% of patients)
Week 1 | 82%
Month 1 | 35% [Eight of the 17 treated patients did not have assessments at Month 1.]
Any assessment [Week 1 or Month 1.] | 94%
IMPROVEMENT [Patients with at least a one-grade improvement in dysphagia grade.] IN DYSPHAGIA (% of patients)
Week 1 | 71%
Month 1 | 47%
Any assessment | 76%
MEAN DYSPHAGIA GRADE [Dysphagia Scale: Grade 1 = normal swallowing; Grade 2 = difficulty swallowing some hard solids, can swallow semisolids; Grade 3 = unable to swallow any solids, can swallow liquids; Grade 4 = difficulty swallowing liquids; Grade 5 = unable to swallow saliva.] AT BASELINE (units) | 4.6
MEAN IMPROVEMENT¶IN DYSPHAGIA GRADE (units)
Week 1 | 1.4
Month 1 | 1.5
MEAN NUMBER OF LASER APPLICATIONS (units) | 1.4

TABLE 11. Efficacy Results from Studies in Late-Stage Obstructing Endobronchial Cancer - All Randomized Patients
EFFICACY PARAMETER | PDT N=102 | Nd:YAG N=109
OBJECTIVE TUMOR RESPONSE [CR+PR where CR = complete response (absence of bronchoscopically visible tumor) and PR = partial response (increase of 50% in the smallest luminal diameter; or any appearance of a lumen for completely obstructing tumors).]
Week 1 | 59% | 58%
Month 1 or later | 60% | 41%a
ATELECASIS IMPROVEMENT [In patients with atelectasis at baseline.] | n=60 | N=71
Week 1 | 35% | 18%
Month 1 or later | 35% | 20%

TABLE 12.Efficacy Results from Studies in Late-stage Obstructing Endobronchial Cancer - Clinically Significant Improvements in Patients with Moderate to Severe Symptoms at Baseline*
CLINICALLY SIGNIFICANT SYMPTOM IMPROVEMENT† | PDT N=102 | Nd:YAG N=109
ANY SYMPTOM | n=89 | n=89
Week 1 | 25% | 29%
Month 1 or later | 40% | 27%a
DYSPNEA | n=60 | n=68
Week 1 | 15% | 18%
Month 1 or later | 23% | 13%
COUGH | n=63 | n=65
Week 1 | 6% | 9%
Month 1 or later | 24% | 8%
HEMOPTYSIS | n=24 | n=31
Week 1 | 58% | 29%
Month 1 or later | 79% | 35%

* Statistical comparisons were precluded by the amount of missing data at Month 1 or later.

† Dyspnea was graded on a 6-point severity rating scale; cough and hemoptysis on a 5-point scale. Clinically significant improvement was defined as a change of at least two grades from baseline.

In a separate retrospective analysis, patients were individually evaluated to identify those patients whose benefit to risk ratio was most favorable, i.e., those who obtained clinically important benefit with minimal adverse reactions. Clinically important benefit was defined as one of the following:

1. A substantial improvement in pulmonary symptoms at Month 1 or later (dyspnea 2 grades, hemoptysis 3 grades, cough 3 grades or increase in FEV1 40%);
2. A moderate improvement in symptoms at Month 2 or later (dyspnea 1 grade, cough 2 grades, hemoptysis 2 grades or increase in FEV1 20%); or
3. A durable objective tumor response (CR or PR maintained to Month 2 or longer).

Thirty-six (36) of the 99 PDT-treated patients (36%) and 23 of the 99 Nd:YAG-treated patients (23%) received clinically important benefit with only minimal or moderate toxicities of short duration. Thirty-four (34) of 99 PDT- treated patients demonstrated improvements in 2 or more efficacy endpoints (dyspnea, cough, hemoptysis, sputum, atelectasis, pulmonary function tests of FEV1 or FVC, Karnofsky Performance Score or tumor response) and 29 patients had improvements in 3 or more.

The median duration of documented benefit in the 36 patients was 63 days. In these patients with late-stage obstructing lung cancer, median survival was 174 days in PDT-treated patients and 161 days in Nd:YAG- treated patients.

The efficacy of PHOTOFRIN PDT was also evaluated in the treatment of microinvasive endobronchial tumors in 62 inoperable patients in three noncomparative studies. Microinvasive lung cancer is defined histologically as disease, which invades beyond the basement membrane but not through or into the cartilage. For 11 of the 62 patients, it was clearly documented that surgery and radiotherapy were not indicated. These 11 patients were all inoperable for medical or technical reasons. Radiotherapy was not indicated due to prior highdose radiotherapy (7 patients), poor pulmonary function (2 patients), multifocal multilobar disease (1 patient), and poor medical condition (1 patient). As shown in Table 13, the complete tumor response rate, biopsy-proven at least 3 months after treatment, was 50%, median time to tumor recurrence was more than 2.7 years, median survival was 2.9 years and disease-specific survival was 4.1 years.

TABLE 13. Overall Efficacy in Patients with Superficial Endobronchial Tumor
EFFICACY PARAMETER | PDT
EFFICACY PARAMETER | n=11 | n=62
COMPLETE TUMOR RESPONSE, BIOPSY-PROVEN AT 3 MONTHS
Number of Patients (%) | 3 (27) | 31 (50) [Not included are an additional 18 patients (6 patients not eligible for surgery or radiotherapy) who had complete tumor responses which were documented earlier than 3 months after treatment.]
TIME TO TUMOR RECURRENCE IN PATIENTS WITH COMPLETE RESPONSE
Number of Patients (%) with Recurrences | 1(33) | 11(35)
Median Time to Tumor Recurrence |  | >2.7 years
[95% Confidence Interval] |  | [1.6, [The upper limit of the confidence interval could not be estimated due to an insufficient number of patients whose tumors recurred (Time to Tumor Recurrence) or who died (Survival).] ]
SURVIVAL
Number of Patients (%) who Died of Any Cause | 4 (36) | 32 (52)
Median Survival |  | 2.9 years
[95% Confidence Interval] |  | [2.1, 5.7]
DISEASE-SPECIFIC SURVIVAL
Number of Patients (%) who Died of Lung Cancer | 3 (27) | 22 (35)
Median Disease-Specific Survival |  | 4.1 years
[95% Confidence Interval] |  | [2.5,†]

14.3 High-Grade Dysplasia in Barrett’s Esophagus

The safety and efficacy of PDT with PHOTOFRIN in ablation of HGD in patients with BE was assessed in one controlled randomized clinical study and two supportive studies.

Controlled Randomized Study

A multicenter, pathology blinded, randomized, controlled study was conducted in North America and Europe to assess the efficacy of PDT with PHOTOFRIN plus omeprazole (PHOTOFRIN PDT + OM) in producing complete ablation of HGD in patients with BE compared to control patients receiving omeprazole alone (OM Only). A total of 485 patients with the diagnosis of HGD were screened for the study; 208 (43%) were randomized to treatment, 237 (49%) were excluded because the diagnosis of HGD was not confirmed and 40 (8%) did not meet other screening criteria or declined to participate in the study.

The high patient exclusion rate re-enforces the recommendation by the American College of Gastroenterology that the diagnosis of HGD in BE should be confirmed by an expert gastrointestinal pathologist. Patients were centrally randomized in a 2:1 proportion to receive PHOTOFRIN PDT + OM (138 patients) or OM Only (70 patients). All patients underwent rigorous systematic quarterly endoscopic biopsy surveillance. Four-quadrant jumbo biopsies at every 2 cm of the entire Barretts mucosa were obtained at each follow-up visit (every three months or six months if four consecutive quarterly follow-up endoscopic biopsy results were negative for HGD). All histological assessments were carried out at a central pathology laboratory and read by pathologists blinded to the treatment administered.

A total of 208 patients who had biopsy-proven HGD in BE were enrolled in the initial 2-year phase of the study. Of those, 199 patients were considered evaluable: 130 of 138 (94%) patients randomized to the PHOTOFRIN PDT + OM group and 69 of 70 (99%) randomized to the OM Only group had no esophageal invasive cancer, suspicion of esophageal invasive cancer, lymph node involvement, or metastases, and had received at least one PHOTOFRIN PDT course or one week of OM treatment, respectively. A disproportionate percentage of patients were discontinued from the OM Only group during the initial 2-year phase leaving 81 (59%) patients in the PHOTOFRIN PDT + OM group and 21 (30%) patients in the OM Only group at the end of the 2-year phase. Consequently, a total of 102 patients who completed the initial 2-year phase were eligible for continuation into the long-term phase until completion of 5 years; of those, 48 (59%) patients from the PHOTOFRIN PDT + OM group and 13 (62%) patients from the OM Only group consented to pursue the long- term phase until completion of 5 years. The mean age was 66 years (38 to 89 years) in the PHOTOFRIN PDT + OM group, and 67 (36 to 88 years) in the OM Only group. The patients in both treatment groups were predominantly male (85%), Caucasian (99%), and former smokers (64%). These characteristics are typical of patients with HGD in BE. Patients randomized to the PHOTOFRIN PDT + OM treatment received up to three courses of treatment separated by at least 90 days. Each course consisted of intravenous administration of 2.0 mg/kg of PHOTOFRIN followed 40-50 hours later by a 630 nm laser light dose of 130 J/cm of diffuser length delivered using a centering balloon. A second laser light dose of 50 J/cm of diffuser length could be administered without a centering balloon 96-120 hours after the injection of PHOTOFRIN for treatment of skip areas. Since centering balloons are up to 7 cm in length, patients with more extensive HGD were treated with two or three courses. Both the PHOTOFRIN PDT treatment group and the control group received 20 mg of omeprazole BID to decrease reflux esophagitis. The mean duration of the follow-up period was 34 months (0- 67 months) for the PHOTOFRIN PDT + OM group and 25 months (0-65 months) for the OM Only group.

The major efficacy outcome measure was the Complete Response rate (CR3 or better) at any one of the endoscopic assessment time points. The CR3 or better response was defined as the complete ablation of HGD and referred to as a composite of the following three response levels.

1. CR1 Complete replacement of all Barretts metaplasia and dysplasia with normal squamous cell epithelium;
2. CR2 Ablation of all histological grades of dysplasia, including patients with indefinite grade of dysplasia, but some areas of Barretts epithelium still remain; and
3. CR3 Ablation of all HGD but with some areas of low-grade dysplasia with or without areas which are indefinite for dysplasia, or areas of Barretts metaplastic epithelium.

Additional efficacy endpoints included:

1. Quality of Complete Response, which consisted of CR1 and CR2 or better.
2. Duration of CR;
3. Time to Progression to Cancer.

Table 14 presents the overall clinical response for both treatment groups in the intent-to-treat (ITT) population whose response was CR3 or better at any one of the evaluation time points. Overall, PHOTOFRIN PDT + OM was effective in eliminating HGD in patients with BE. The proportion of responders was significantly higher in the PHOTOFRIN PDT + OM group than in the OM Only group (77% vs. 39%, respectively; p<0.0001).

The quality of response in the PHOTOFRIN PDT + OM group was significantly better than that measured in the OM Only group at all response levels (p<0.0001). Seventy-two (52%) patients in the PHOTOFRIN PDT + OM group achieved a CR1 response as compared to only five (7%) patients in the OM Only group. Eighty-one (59%) patients in the PHOTOFRIN PDT + OM group achieved a CR2 or better response as compared to ten (14%) patients in the OM Only group.

TABLE 14. Complete Response Rates After a Minimum Follow-Up of 24 Months in the ITT Population
Responders | TREATMENT GROUPS
Responders | PHOTOFRIN PDT+OM N=138 | OM Only N=70 | p-value*
CR3 or better† | n = 106 | n= 27
Proportion (%) 95% CI | 0.768 (76.8) | 0.386 (38.6) | <0.0001
Proportion (%) 95% CI | (0.689, 0.836) | (0.272, 0.510)

* Fishers Exact test.

† CR3 or better: Ablation of all areas of HGD.

NOTE: Six patients in the PHOTOFRIN PDT + OM group and three patients in the OM Only group without post-baseline biopsy data are considered as non-responders.

At the end of the long-term phase, the median response duration was 44.6 months (95% CI: 15.0-not reached, months) in the PHOTOFRIN PDT + OM group compared to 3.2 months (95% CI: 3.0- 3.4, months) in the OM Only group.

At the end of the initial 2 year phase, the time to progression to cancer was significantly longer in the PHOTOFRIN PDT + OM group compared to the OM Only group (HR=0.36 (95% CI: 0.19-0.69), a hazard ratio less than 1 favors the PHOTOFRIN PDT + OM group). The proportion of patients progression to cancer was lower in the PHOTOFRIN PDT + OM group than in the OM Only group: 13% (18 of 138 patients) vs. 28% (20 of 70 patients).

Complete response was influenced by the following factors: treatment with PHOTOFRIN PDT + OM (vs. OM Only), single focus of HGD (vs. multiple foci), and prior omeprazole intake of at least 3 months (yes vs. no). Complete response was not influenced by the duration of HGD, length of BE, nodular conditions, gender, age, smoking history, and study centers size.

Supportive Studies

Two uncontrolled, supportive studies were conducted that were physician-sponsored, single center Phase II trials. Both studies included patients that had low-grade dysplasia (LGD), HGD and early adenocarcinoma. All HGD in BE patients were treated with PHOTOFRIN PDT and omeprazole.

The first study enrolled 99 patients (44 with HGD); the purpose of this study was to determine the required light dose to produce effective results. The second study enrolled 86 patients (42 with HGD), who were randomized to receive either PHOTOFRIN PDT with prednisone or PHOTOFRIN PDT without prednisone to determine whether steroid treatment would reduce the incidence and severity of esophageal strictures.

A CR3 or better response was demonstrated in 93% of 44 patients with HGD in the first study and in 95% of 42 patients with HGD in the second study after a minimum follow-up of 12 months. A CR2 or better response was achieved in 82% of patients in the first study and in 91% of patients in the second study. A CR1 response occurred in 57% of patients in the first study and in 60% of the second study. Progression to cancer during the above follow-up period occurred in 18% of patients in the first study and in 7% of patients in the second study. No reduction in the incidence or severity of esophageal strictures was found in the prednisone group in the second study.

16 HOW SUPPLIED/STORAGE AND HANDLING

PHOTOFRIN (porfimer sodium) for Injection is supplied as a lyophilized powder as follows:

NDC 76128-155-75, 75 mg single-dose vial.

Storage

Store at Controlled Room Temperature 20°C to 25°C (68°F to 77°F); excursions permitted to 15°C to 30°C (59°F to 86°F) [see USP Controlled Temperature].

Spills and Disposal

Spills of PHOTOFRIN should be wiped up with a damp cloth. Skin and eye contact should be avoided due to the potential for photosensitivity reactions upon exposure to light; use of rubber gloves and eye protection is recommended. All contaminated materials should be disposed of in a polyethylene bag in a manner consistent with local regulations.

Accidental Exposure

PHOTOFRIN is neither a primary ocular irritant nor a primary dermal irritant. However, because of its potential to induce photosensitivity, PHOTOFRIN might be an eye and/or skin irritant in the presence of bright light. It is important to avoid contact with the eyes and skin during preparation and/or administration. As with therapeutic overdosage, any overexposed person must be protected from bright light.

17 PATIENT COUNSELING INFORMATION

Photosensitivity

Advise patients to avoid exposure of skin and eyes to direct sunlight or bright indoor light for at least 30 days following PHOTOFRIN [see Warnings and Precautions (5.4, 5.5)] .

Inform patients that photosensitivity might last for more than 90 days if patients suffer from renal or hepatic impairment.

Instruct patients to wear protective clothing and dark sunglasses when outdoors, which have an average white light transmittance of < 4%.

Encourage patients to expose their skin to ambient indoor light to facilitate elimination of PHOTOFRIN from their skin.

Common Adverse Reactions

Inform patients that treatment with PHOTOFRIN and photodynamic therapy might lead to adverse reactions which include chest pain, respiratory distress or esophageal strictures [see Warnings and Precautions (5.7, 5.8, 5.9)]. Advise patients to contact their healthcare providers for new or worsening adverse reactions).

Embryo-Fetal Toxicity

Advise pregnant women of the potential risk to a fetus. Advise females of reproductive potential to inform their healthcare provider of a known or suspected pregnancy [see Warnings and Precautions (5.12), Use in Specific Populations (8.1)] .

Advise females of reproductive potential to use effective contraception during treatment with PHOTOFRIN and for 5 months after the final dose [see Use in Specific Populations (8.3)] .

Advise male patients with female partners of reproductive potential to use condoms during treatment with PHOTOFRIN and for 5 months following the final dose [see Use in Specific Populations (8.3), Nonclinical Toxicology (13.1)] .

Lactation

Advise women not to breastfeed during treatment with PHOTOFRIN and for 5 months after the last dose [see Use in Specific Populations (8.2)].

Distributed by:

Pinnacle Biologics, Inc.,
2801 Lakeside Drive, Suite 210
Bannockburn, IL 60015

PINN-204 v2

Vial Label Panel

NDC 76128-155-75

PHOTOFRIN
(porfimer sodium) for injection

75 mg Single-Dose Vial

For Intravenous Use Only

Contains No Preservatives

For dosage and administration,
see package insert.

Rx ONLY

Carton Label Panel

NDC 76128-155-75

PHOTOFRIN
(porfimer sodium) for injection

75 mg Single-Dose Vial

For Intravenous Use Only

Contains No Preservatives

For dosage and administration,
see package insert.

Rx ONLY

PINNACLE

www.pinnaclebiologics.com